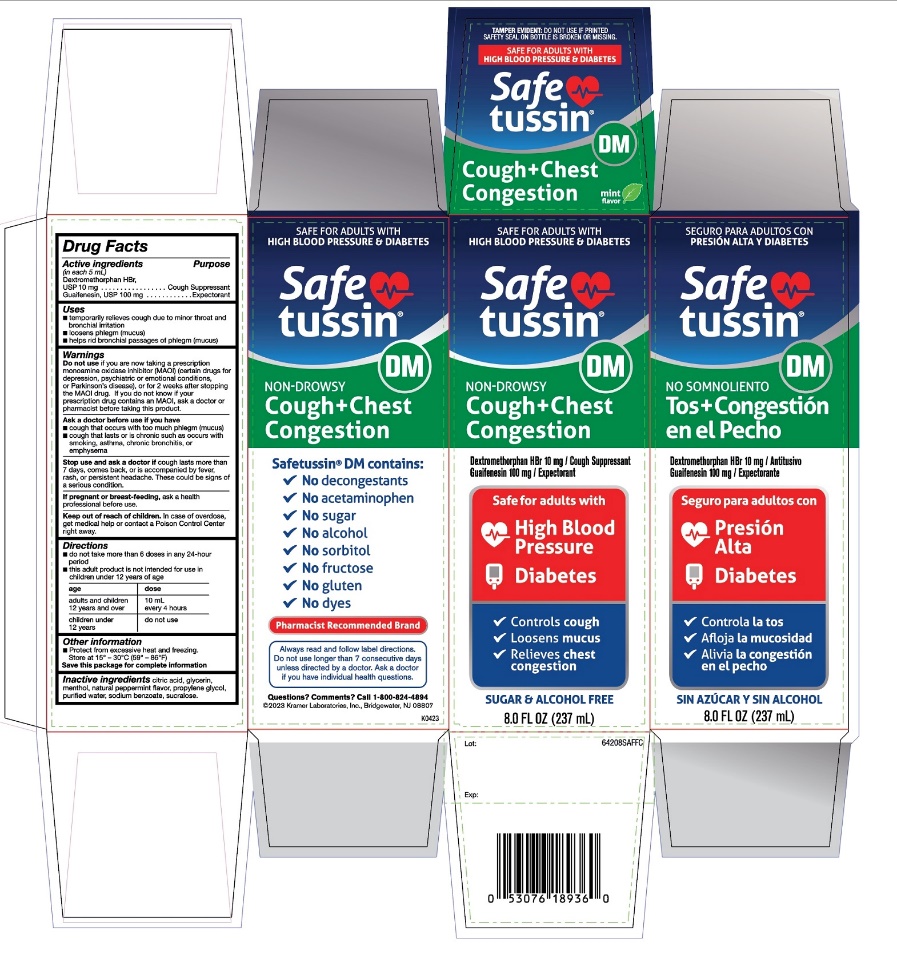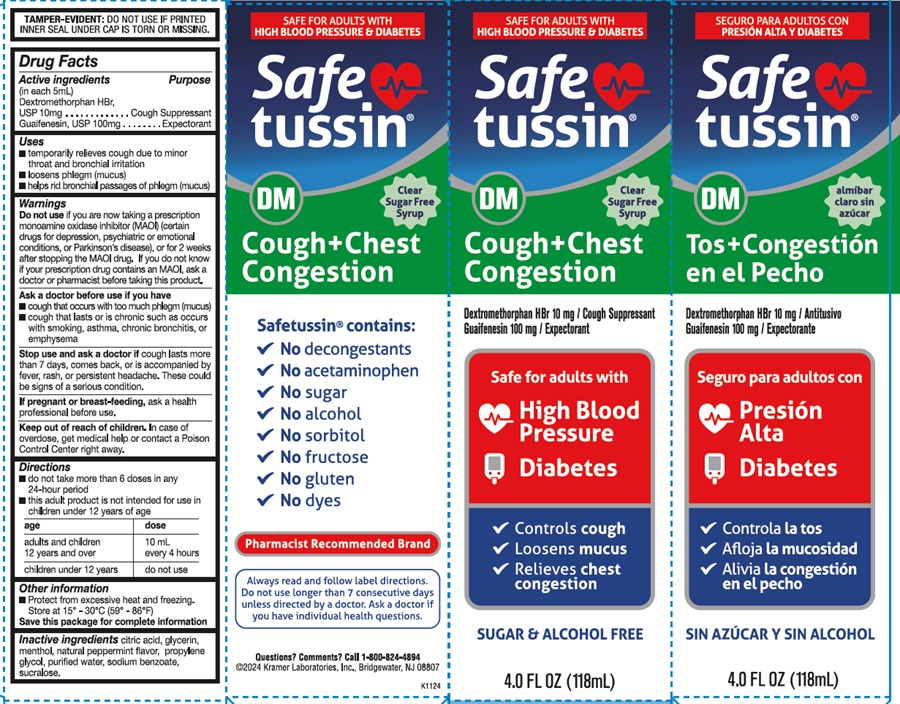 DRUG LABEL: SAFETUSSIN Non Drowsy
NDC: 55505-220 | Form: LIQUID
Manufacturer: KRAMER LABORATORIES
Category: otc | Type: HUMAN OTC DRUG LABEL
Date: 20250611

ACTIVE INGREDIENTS: DEXTROMETHORPHAN HYDROBROMIDE 10 mg/5 mL; GUAIFENESIN 100 mg/5 mL
INACTIVE INGREDIENTS: CITRIC ACID MONOHYDRATE; GLYCERIN; MENTHOL, UNSPECIFIED FORM; MINT; PROPYLENE GLYCOL; WATER; SODIUM BENZOATE; SUCRALOSE

SAFETUSSIN Non-Drowsy Cough and chest Drug Facts

Drug Facts

ACTIVE INGREDIENT

Active ingredients (in each 5 mL) | Purpose
Dextromethorphan HBr 10 mg | Cough suppressant
Guaifenesin 100 mg | Expectorant

Uses

- temporarily relieves cough due to minor throat and bronchial irritation
- loosen phlegm (mucus)
- helps rid bronchial passages of phlegm(mucus)

Warnings

Do not use

- if you are now taking a prescription monoamine oxidase inhibitor (MAOI) (certain drugs for depression, psychiatric or emotional conditions, or Parkinson's disease), or for 2 weeks after stopping the MAOI drug. If you do not know if your prescription drug contains an MAOI, ask a doctor or pharmacist before taking this product.

Ask a doctor before use if you have

- cough that occurs with too much phlegm (mucus)
- cough that lasts or is chronic such as occurs with smoking, asthma, chronic bronchitis or emphysema

Stop use and ask a doctor if

cough lasts more than 7 days, comes back, or is accompanied by fever, rash, or persistent headache.
  These could be signs of a serious condition.

PREGNANCY OR BREAST FEEDING

If pregnant or breast-feeding, ask a health professional before use.

Keep out of reach of children. In case of overdose, get medical help or contact a Poison Control Center right away.

Directions

- do not take more than 6 doses in any 24-hours period
- This adult product is not intended for use in children under 12 years of age

age | dose
Adults and children 12 years and over | 10 mL every 4 hours
Children under 12 years | do not use

Other information

- Protect from excessive heat and freezing.
  Store at 15° - 30°C (59° - 86°F)

Save this package for complete information

Inactive ingredients

citric acid, glycerin, menthol, natural peppermint flavor, propylene glycol, purified water, sodium benzoate, sucralose,

Questions? Comments?

Call 1-800-824-4894

Distributed by

©2023 Kramer Laboratories, Inc Bridgewater, NJ 08807

PRINCIPAL DISPLAY PANEL - 237 ml Bottle Label

SAFE FOR ADULTS WITH
HIGH BLOOD PRESSURE & DIABETES
Safe
tussin®
DM
NON-DROWSY
Cough + Chest
Congestion
Dextromethorphan HBr 10mg / Cough Suppressant
Guaifenesin 100mg / Expectorant
Safe for adults with
● High Blood Pressure
● Diabetes
✓ Controls cough
✓ Loosens mucus
✓ Relieves chest congestion
SUGAR & ALCOHOL FREE
8.0 FL OZ (237mL)
SEGURO PARA ADULTOS CON
PRESIÓN ALTA Y DIABETES
Safe
tussin®
DM
NO SOMNOLIENTO
Tos + Congestión
en el Pecho
Dextromethorphan HBr 10mg / Antitusivo
Guaifenesin 100mg / Expectorante
Seguro para adultos con
● Presión Alta
● Diabetes
✓ Controla la tos
✓ Afloja la muscosidad
✓ Alivia la congestion en el pecho
SIN AZÚCAR Y SIN ALCOHOL
8.0 FL OZ (237mL)
SAFE FOR ADULTS WITH
HIGH BLOOD PRESSURE & DIABETES
Safe
tussin®
DM
NON-DROWSY
Cough + Chest
Congestion
Safetussin® contains:
✓ No decongestants
✓ No acetaminophen
✓ No sugar
✓ No alcohol
✓ No sorbitol
✓ No fructose
✓ No gluten
✓ No dyes
Pharmacist Recommended Brand
Always read and follow label directions.
Do not use longer than 7 consecutive days
unless directed by a doctor. Ask a doctor
if you have individual health questions.
Questions? Comments? Call 1-800-824-4894
©2020 Kramer Laboratories, Inc., Bridgewater, NJ 08807
K0423

PRINCIPAL DISPLAY PANEL - 118 ml Bottle Label

SAFE FOR ADULTS WITH
HIGH BLOOD PRESSURE & DIABETES
Safe
tussin®
DM
clear
sugar free
syrup
Cough + Chest
Congestion
Dextromethorphan HBr 10mg / Cough Suppressant
Guaifenesin 100mg / Expectorant
Safe for adults with
● High Blood Pressure
● Diabetes
✓ Controls cough
✓ Loosens mucus
✓ Relieves chest congestion
SUGAR & ALCOHOL FREE
4.0 FL OZ (118mL)
SEGURO PARA ADULTOS CON
PRESIÓN ALTA Y DIABETES
Safe
tussin®
DM
almíbar
claro sin
azúcar
Tos + Congestión
en el Pecho
Dextromethorphan HBr 10mg / Antitusivo
Guaifenesin 100mg / Expectorante
Seguro para adultos con
● Presión Alta
● Diabetes
✓ Controla la tos
✓ Afloja la muscosidad
✓ Alivia la congestion en el pecho
SIN AZÚCAR Y SIN ALCOHOL
4.0 FL OZ (118mL)
SAFE FOR ADULTS WITH
HIGH BLOOD PRESSURE & DIABETES
Safe
tussin®
DM
clear
sugar free
syrup
Cough + Chest Congestion
Safetussin® contains:
✓ No decongestants
✓ No acetaminophen
✓ No sugar
✓ No alcohol
✓ No sorbitol
✓ No fructose
✓ No gluten
✓ No dyes
Pharmacist Recommended Brand
Always read and follow label directions.
Do not use longer than 7 consecutive days
unless directed by a doctor. Ask a doctor if
you have individual health questions.
Questions? Comments? Call 1-800-824-4894
©2020 Kramer Laboratories, Inc., Bridgewater, NJ 08807
K1124
TAMPER-EVIDENT: DO NOT USE IF PRINTED
INNER SEAL UNDER CAP IS TORN OR MISSING.